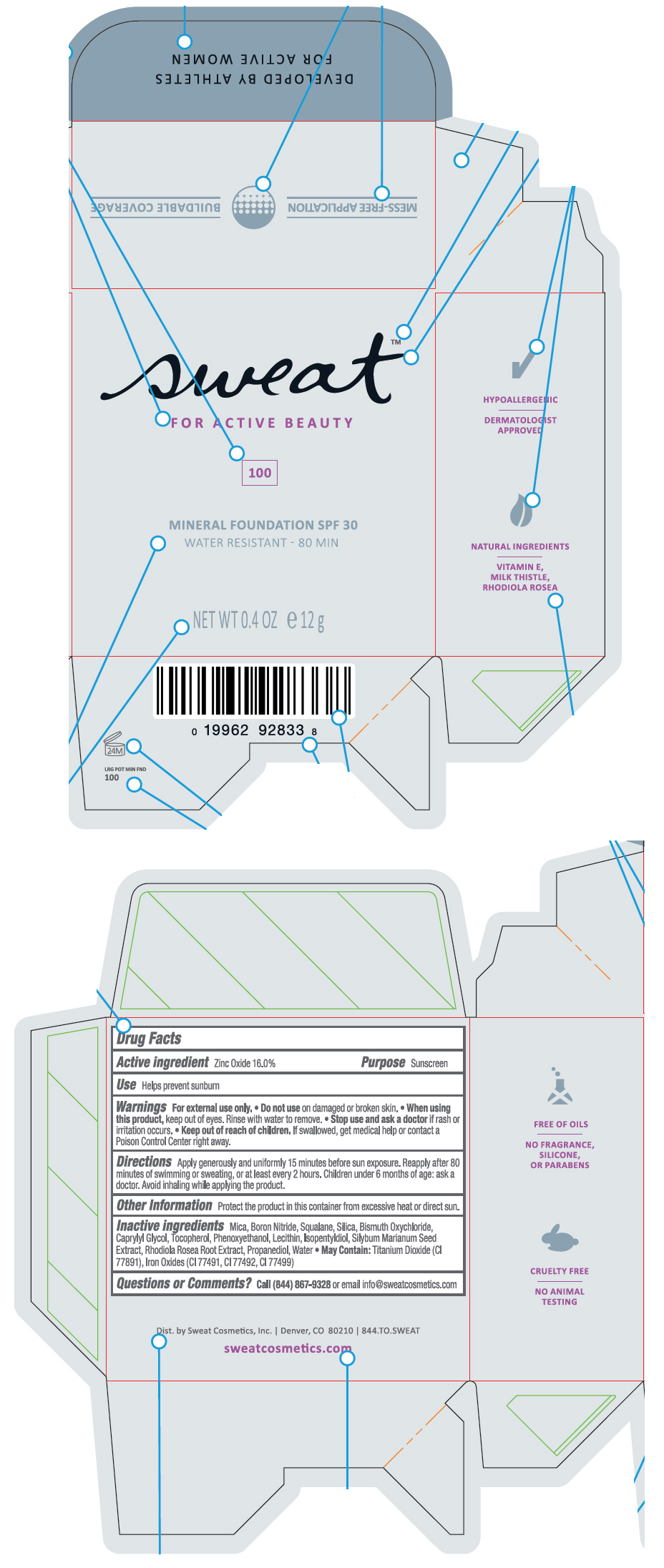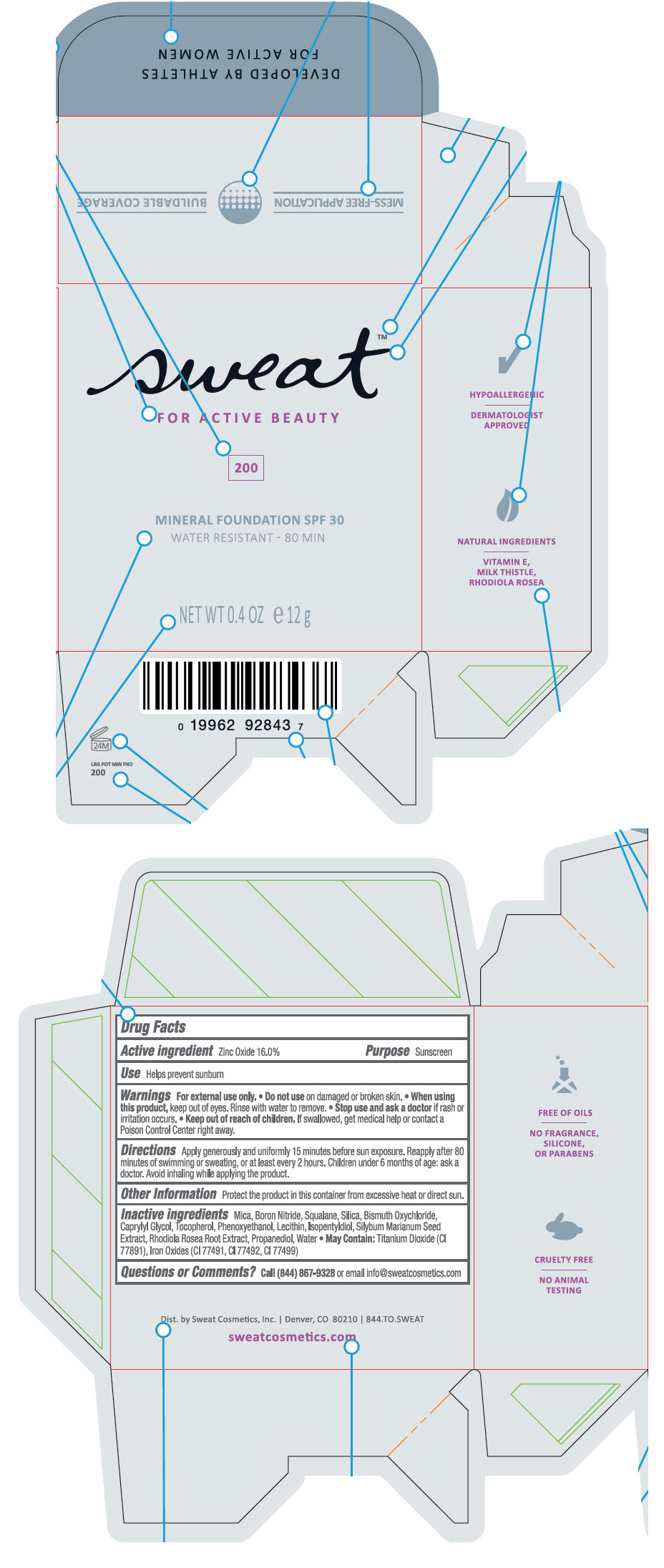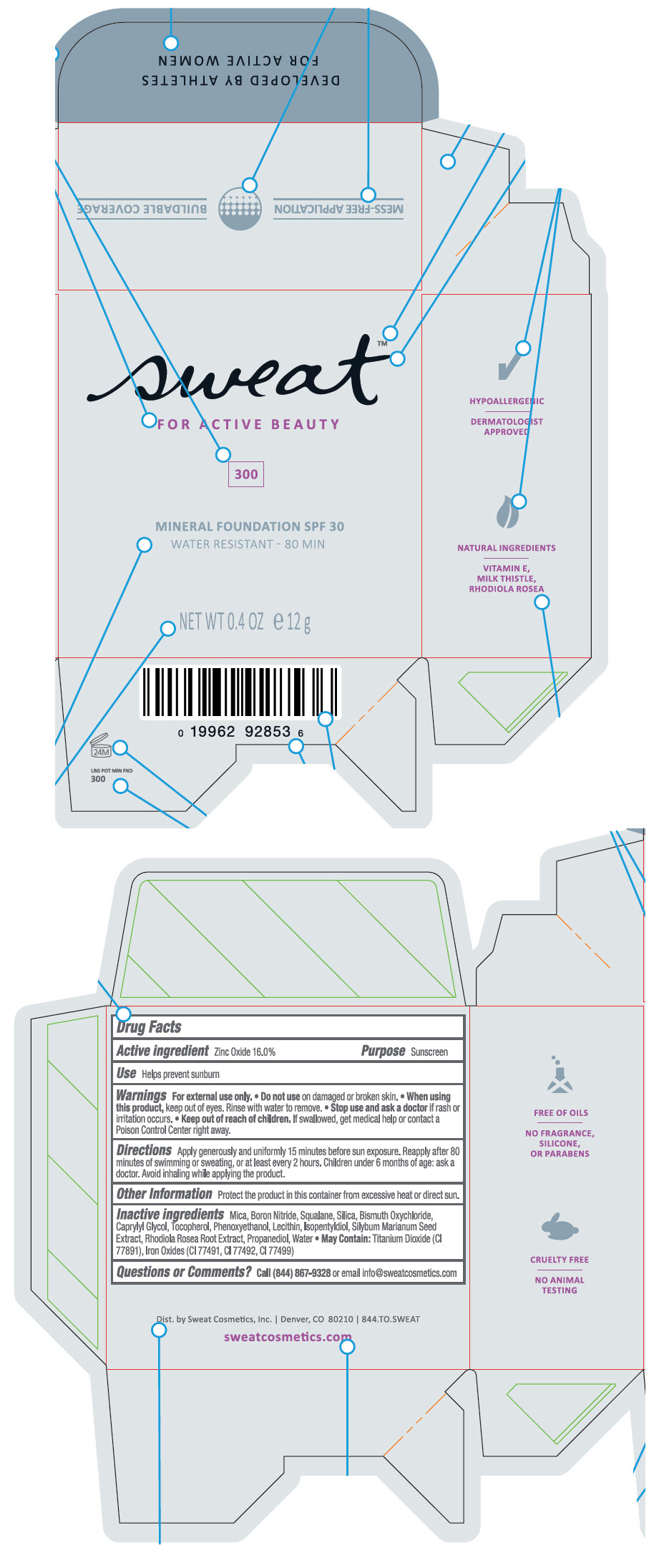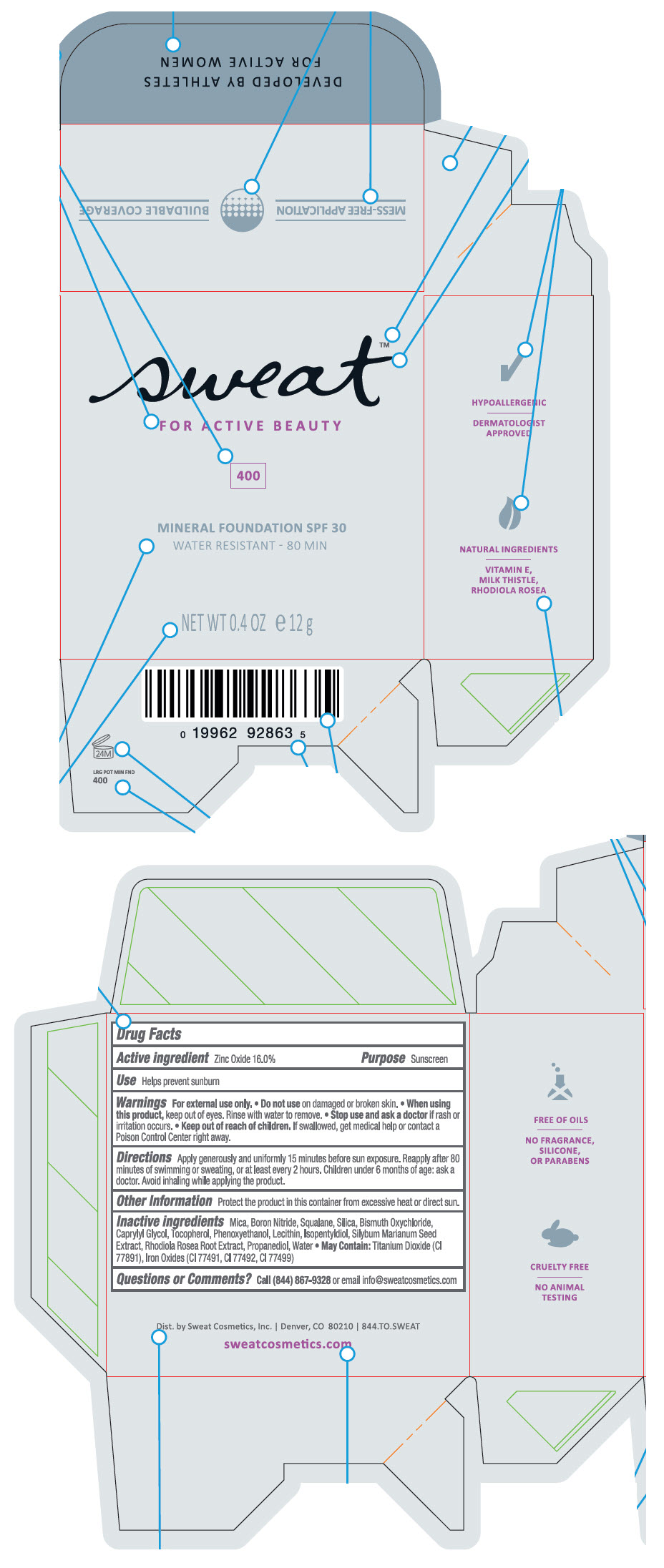 DRUG LABEL: Sweat Mineral Foundation SPF 30 
NDC: 80449-100 | Form: POWDER
Manufacturer: Sweat Cosmetics, Inc.
Category: otc | Type: HUMAN OTC DRUG LABEL
Date: 20200911

ACTIVE INGREDIENTS: Zinc Oxide 16 g/100 g
INACTIVE INGREDIENTS: MICA; BORON NITRIDE; SQUALANE; SILICON DIOXIDE; BISMUTH OXYCHLORIDE; CAPRYLYL GLYCOL; TOCOPHEROL; PHENOXYETHANOL; ISOPENTYLDIOL; MILK THISTLE; SEDUM ROSEUM ROOT; PROPANEDIOL; WATER; TITANIUM DIOXIDE; FERRIC OXIDE RED; FERRIC OXIDE YELLOW; FERROSOFERRIC OXIDE

Sweat™ Mineral Foundation SPF 30

Drug Facts

Active Ingredients

Zinc Oxide 16%

Purpose

Sunscreen

Use

Helps prevent sunburn

Warnings

For external use only.

- Do not use on damaged or broken skin.
- When using this product, keep out of eyes. Rinse with water to remove.
- Stop use and ask doctor if rash or irritation occurs.

- Keep out of reach of children. If swallowed, get medical help or contact a Poison Control Center right away.

Directions

Apply generously and uniformly 15 minutes before sun exposure. Reapply after 80 minutes of swimming or sweating, or at least every 2 hours. Children under 6 months of age: ask a doctor. Avoid inhaling while applying the product.

Other Information

Protect the product in this container from excessive heat or direct sun.

Inactive Ingredients

Mica, Boron Nitride, Squalane, Silica, Bismuth Oxychloride, Caprylyl Glycol, Tocopherol, Phenoxyethanol, Lecithin, Isopentyldiol, Silybum Marianum Seed Extract, Rhodiola Rosea Root Extract, Propanediol, Water

- May Contain: Titanium Dioxide (Cl 77891), Iron Oxides (Cl 77491, Cl 77492, Cl 77499)

Questions or Comments?

Call (844) 867-9328 or email info@sweatcosmetics.com

Dist. by Sweat Cosmetics, Inc. | Denver, CO 80210

PRINCIPAL DISPLAY PANEL - 12 g Jar Box - 100

sweat™

FOR ACTIVE BEAUTY

100

MINERAL FOUNDATION SPF 30
WATER RESISTANT - 80 MIN

NET WT 0.4 OZ ℮ 12 g

PRINCIPAL DISPLAY PANEL - 12 g Jar Box - 200

sweat™

FOR ACTIVE BEAUTY

200

MINERAL FOUNDATION SPF 30
WATER RESISTANT - 80 MIN

NET WT 0.4 OZ ℮ 12 g

PRINCIPAL DISPLAY PANEL - 12 g Jar Box - 300

sweat™

FOR ACTIVE BEAUTY

300

MINERAL FOUNDATION SPF 30
WATER RESISTANT - 80 MIN

NET WT 0.4 OZ ℮ 12 g

PRINCIPAL DISPLAY PANEL - 12 g Jar Box - 400

sweat™

FOR ACTIVE BEAUTY

400

MINERAL FOUNDATION SPF 30
WATER RESISTANT - 80 MIN

NET WT 0.4 OZ ℮ 12 g